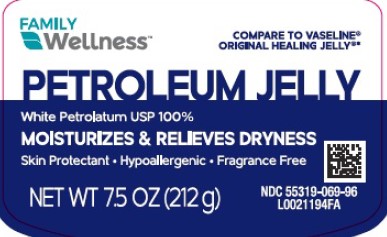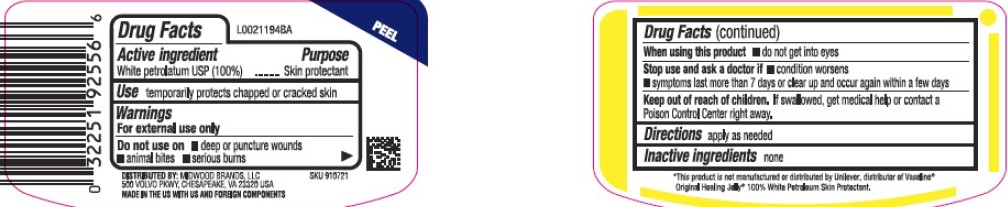 DRUG LABEL: Petroleum Skin Protectant
NDC: 55319-069 | Form: JELLY
Manufacturer: Family Dollar Stores, Inc
Category: otc | Type: HUMAN OTC DRUG LABEL
Date: 20260224

ACTIVE INGREDIENTS: PETROLATUM 1 g/1 g

Family Wellness 069.001/069AA
Petroleum Jelly

Active ingredient

White petrolatum USP (100%)

Purpose

Skin protectant

Use

temporarily protects chapped and cracked skin

Warnings

For external use only

Do not use on

- deep or puncture wounds
- animal bites
- serious burns

When using this product

- do not get into eyes

Stop use and ask a doctor if

- condition worsens
- symptoms last more than 7 days or clear up and occur again within a few days

Keep out of reach of children.

If swallowed, get medical help or contact a Poison Control Center right away.

Directions

apply as needed

Inactive ingredients

None

Disclaimer

*This product is not manufactured or distributed by Unilever, distributor of Vaseline® Original Healing Jelly® 100% White Pteroleum Skin Protectant.

Adverse Reaction

Distributed By: Midwood Brands, LLC

500 Volvo PKWY, Chesapeake, VA 23320 USA

MADE IN THE US WITH US AND FOREIGN COMPONENTS

Principal display panel

FAMILY WELLNESS™

COMPARE TO VASELINE® ORIGINAL HEALING JELLY®*

PETROLEUM JELLY

White Petroleum, 100%

MOISTURIZES & RELIEVES DRYNESS

- Skin Protectant
- Hypoallergenic
- Fragrance Free

NDC 55319-069-96

NET WT 7.5 OZ (212 g)